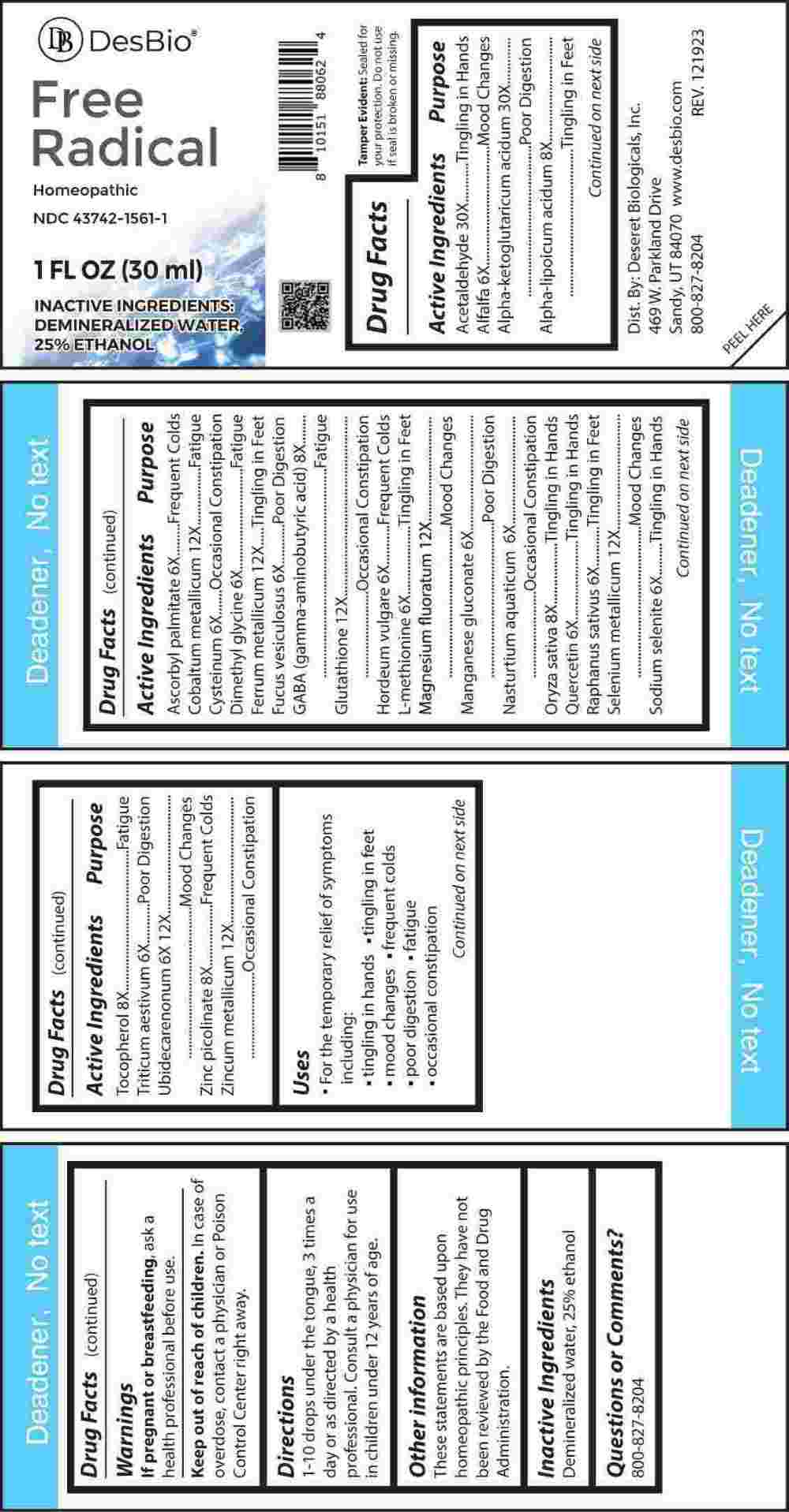 DRUG LABEL: Free Radical
NDC: 43742-1561 | Form: LIQUID
Manufacturer: Deseret Biologicals, Inc.
Category: homeopathic | Type: HUMAN OTC DRUG LABEL
Date: 20240404

ACTIVE INGREDIENTS: MEDICAGO SATIVA WHOLE 6 [hp_X]/1 mL; ASCORBYL PALMITATE 6 [hp_X]/1 mL; CYSTEINE 6 [hp_X]/1 mL; N,N-DIMETHYLGLYCINE 6 [hp_X]/1 mL; FUCUS VESICULOSUS 6 [hp_X]/1 mL; BARLEY 6 [hp_X]/1 mL; METHIONINE 6 [hp_X]/1 mL; MANGANESE GLUCONATE 6 [hp_X]/1 mL; NASTURTIUM OFFICINALE 6 [hp_X]/1 mL; QUERCETIN 6 [hp_X]/1 mL; RAPHANUS SATIVUS 6 [hp_X]/1 mL; SODIUM SELENITE 6 [hp_X]/1 mL; WHEAT 6 [hp_X]/1 mL; UBIDECARENONE 6 [hp_X]/1 mL; .ALPHA.-LIPOIC ACID 8 [hp_X]/1 mL; .GAMMA.-AMINOBUTYRIC ACID 8 [hp_X]/1 mL; ORYZA SATIVA WHOLE 8 [hp_X]/1 mL; .ALPHA.-TOCOPHEROL 8 [hp_X]/1 mL; ZINC PICOLINATE 8 [hp_X]/1 mL; COBALT 12 [hp_X]/1 mL; IRON 12 [hp_X]/1 mL; GLUTATHIONE 12 [hp_X]/1 mL; MAGNESIUM FLUORIDE 12 [hp_X]/1 mL; SELENIUM 12 [hp_X]/1 mL; ZINC 12 [hp_X]/1 mL; ACETALDEHYDE 30 [hp_X]/1 mL; .ALPHA.-KETOGLUTARIC ACID 30 [hp_X]/1 mL
INACTIVE INGREDIENTS: WATER; ALCOHOL

DRUG FACTS:

ACTIVE INGREDIENTS:

Acetaldehyde 30X, Alfalfa 6X, Alpha-Ketoglutaricum Acidum 30X, Alpha-Lipoicum Acidum 8X, Ascorbyl Palmitate 6X, Cobaltum Metallicum 12X, Cysteinum 6X, Dimethyl Glycine 6X, Ferrum Metallicum 12X, Fucus Vesiculosus 6X, GABA (Gamma Aminobutyric Acid) 8X, Glutathione 12X, Hordeum Vulgare 6X, L-Methionine 6X, Magnesium Fluoratum 12X, Manganese Gluconate 6X, Nasturtium Aquaticum 6X, Oryza Sativa 8X, Quercetin 6X, Raphanus Sativus 6X, Selenium Metallicum 12X, Sodium Selenite 6X, Tocopherol 8X, Triticum Aestivum 6X, Ubidecarenonum 6X, 12X, Zinc Picolinate 8X, Zincum Metallicum 12X.

PURPOSE:

Acetaldehyde – Tingling in Hands, Alfalfa – Mood Changes, Alpha-Ketoglutaricum Acidum – Poor Digestion, Alpha-Lipoicum Acidum – Tingling in Feet, Ascorbyl Palmitate – Frequent Colds, Cobaltum Metallicum - Fatigue, Cysteinum – Occasional Constipation, Dimethyl Glycine - Fatigue, Ferrum Metallicum – Tingling in Feet, Fucus Vesiculosus – Poor Digestion, GABA (Gamma Aminobutyric Acid) - Fatigue, Glutathione – Occasional Constipation, Hordeum Vulgare – Frequent Colds, L-Methionine – Tingling in Feet, Magnesium Fluoratum – Mood Changes, Manganese Gluconate – Poor Digestion, Nasturtium Aquaticum – Occasional Constipation, Oryza Sativa – Tingling in Hands, Quercetin – Tingling in Hands, Raphanus Sativus – Tingling in Feet, Selenium Metallicum – Mood Changes, Sodium Selenite – Tingling in Hands, Tocopherol - Fatigue, Triticum Aestivum – Poor Digestion, Ubidecarenonum – Mood Changes, Zinc Picolinate – Frequent Colds, Zincum Metallicum – Occasional Constipation

USES:

• For the temporary relief of symptoms including:

• tingling in hands • tingling in feet • mood changes

• frequent colds • poor digestion • fatigue • occasional constipation

These statements are based upon homeopathic principles. They have not been reviewed by the Food and Drug Administration.

WARNINGS:

If pregnant or breast-feeding, ask a health professional before use.

Keep out of reach of children. In case of overdose, contact a physician or a Poison Control Center right away.

Tamper Evident: Sealed for your protection. Do not use if seal is broken or missing.

KEEP OUT OF REACH OF CHILDREN:

In case of overdose, contact a physician or Poison Control Center right away.

DIRECTIONS:

1-10 drops under the tongue, 3 times a day or as directed by a health professional. Consult a physician for use in children under 12 years of age.

INACTIVE INGREDIENTS:

Demineralized water, 25% ethanol

QUESTIONS:

Dist. By: Deseret Biologicals, Inc.

469 W. Parkland Drive

Sandy, UT 84070

www.desbio.com

800-827-8204

PACKAGE LABEL DISPLAY:

Des Bio

Free Radical

Homeopathic

NDC 43742-1561-1

1 FL OZ (30 ml)